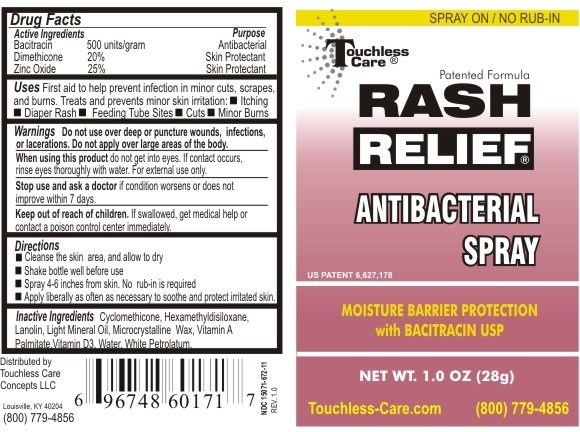 DRUG LABEL: Rash Relief Antibacterial
NDC: 15071-672 | Form: LIQUID
Manufacturer: Touchless Care Concepts LLC
Category: otc | Type: HUMAN OTC DRUG LABEL
Date: 20111116

ACTIVE INGREDIENTS: Bacitracin 500 [iU]/1 g; Dimethicone 20 g/100 g; Zinc Oxide 25 g/100 g
INACTIVE INGREDIENTS: Cyclomethicone; Mineral Oil; Lanolin; Microcrystalline Wax; Hexamethyldisiloxane; Water; Cholecalciferol; Vitamin a palmitate; Petrolatum

RASH RELIEF ANTIBACTERIAL SPRAY

Active Ingredients

Bacitracin 500 units/g

Dimethicone 20%

Petrolatum 25%

Purpose

Antibacterial / Skin Protectant

Warnings

- Do not use over deep or puncture wounds, infections, or lacerations. Do not apply over large areas of the body.

- When using this product do not get into eyes. If contact occurs, rinse eyes thoroughly with water. For external use only.

- Stop use and ask a doctor if condition worsens or does not improve in 7 days..

Directions

- Cleanse the skin area, and allow to dry.

- Shake bottle well before use.

- Spray 4-6 inches from skin. No rub-in is required.

- Apply liberally as often as necessary to soothe and protect irritated skin.

Inactive Ingredients

Cyclomethicone, Hexamethyldisiloxane, Lanolin, Light Mineral Oil, Microcrystalline Wax, Vitamin A Palmitate, Vitamin D3, Water, White Petrolatum

- Keep out of reach of children. If swallowed, get medical help or contact a local poison control center immediately.

INDICATIONS AND USAGE

Uses: First aid to help prevent infection in minor cuts, scrapes, and burns. Treats and prevents minor skin irritation: itching, diaper rash, feeding tube sites, cuts, and minor burns.

PACKAGE LABEL

Enter section text here